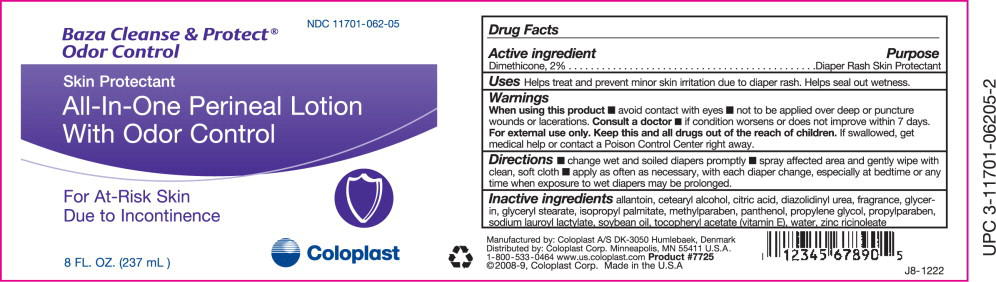 DRUG LABEL: Baza Cleanse and Protect Odor Control
NDC: 11701-062 | Form: LOTION
Manufacturer: Coloplast Manufacturing US, LLC
Category: otc | Type: HUMAN OTC DRUG LABEL
Date: 20231221

ACTIVE INGREDIENTS: DIMETHICONE 20 mg/1 g
INACTIVE INGREDIENTS: GLYCERYL MONOSTEARATE; CETOSTEARYL ALCOHOL; ISOPROPYL PALMITATE; .ALPHA.-TOCOPHEROL ACETATE, D-; SOYBEAN OIL; ZINC RICINOLEATE; CITRIC ACID MONOHYDRATE; PANTHENOL; GLYCERIN; METHYLPARABEN; PROPYLPARABEN; SODIUM LAUROYL LACTYLATE; PROPYLENE GLYCOL; DIAZOLIDINYL UREA; ALLANTOIN; WATER

Baza Cleanse & Protect®
Odor Control
Skin Protectant
All-In-One Perineal Lotion
With Odor Control

For At-Risk Skin Due to Incontinence

Drug Facts

Active ingredient

Dimethicone, 2%

Purpose

Diaper Rash Skin Protectant

INDICATIONS AND USAGE

Uses Helps treat and prevent minor skin irritation due to diaper rash. Helps seal out wetness.

Warnings

When using this product

- avoid contact with eyes
- not to be applied over deep or puncture wounds or lacerations.

Consult a doctor

- if condition worsens or does not improve within 7 days.

For external use only.

KEEP OUT OF REACH OF CHILDREN

Keep this and all drugs out of the reach of children. If swallowed, get medical help or contact a Poison Control Center right away.

Directions

- change wet and soiled diapers promptly
- spray affected area and gently wipe with clean, soft cloth
- apply as often as necessary, with each diaper change, especially at bedtime or any time when exposure to wet diapers may be prolonged.

INACTIVE INGREDIENT

Inactive ingredients allantoin, cetearyl alcohol, citric acid, diazolidinyl urea, fragrance, glycerin, glyceryl stearate, isopropyl palmitate, metfiylparaben, panthenol, propylene glycol, propylparaben, sodium laurovl lactvlate. soybean oil. tocoDhervl acetate (vitamin B. water, zinc ricinoleate

Manufactured by: Coloplast A/S DK-3050 Humlebaek, Denmark
Distributed by: Coloplast Corp. Minneapolis, MN 55411 U.S.A.
1-800-533-0464 www.us.coloplast.com Product #7725
©2008-9, Coloplast Corp. Made in the U.S.A

J8-1222

PACKAGE LABEL

PRINCIPAL DISPLAY PANEL - 8 FL. OZ. (237 mL)

NDC 11701-062-05

Baza Cleanse & Protect® Odor Control

Skin Protectant

All-In-One Perineal Lotion With Odor Control

For At-Risk Skin Due to Incontinence

Coloplast

8 FL. OZ. (237 mL)